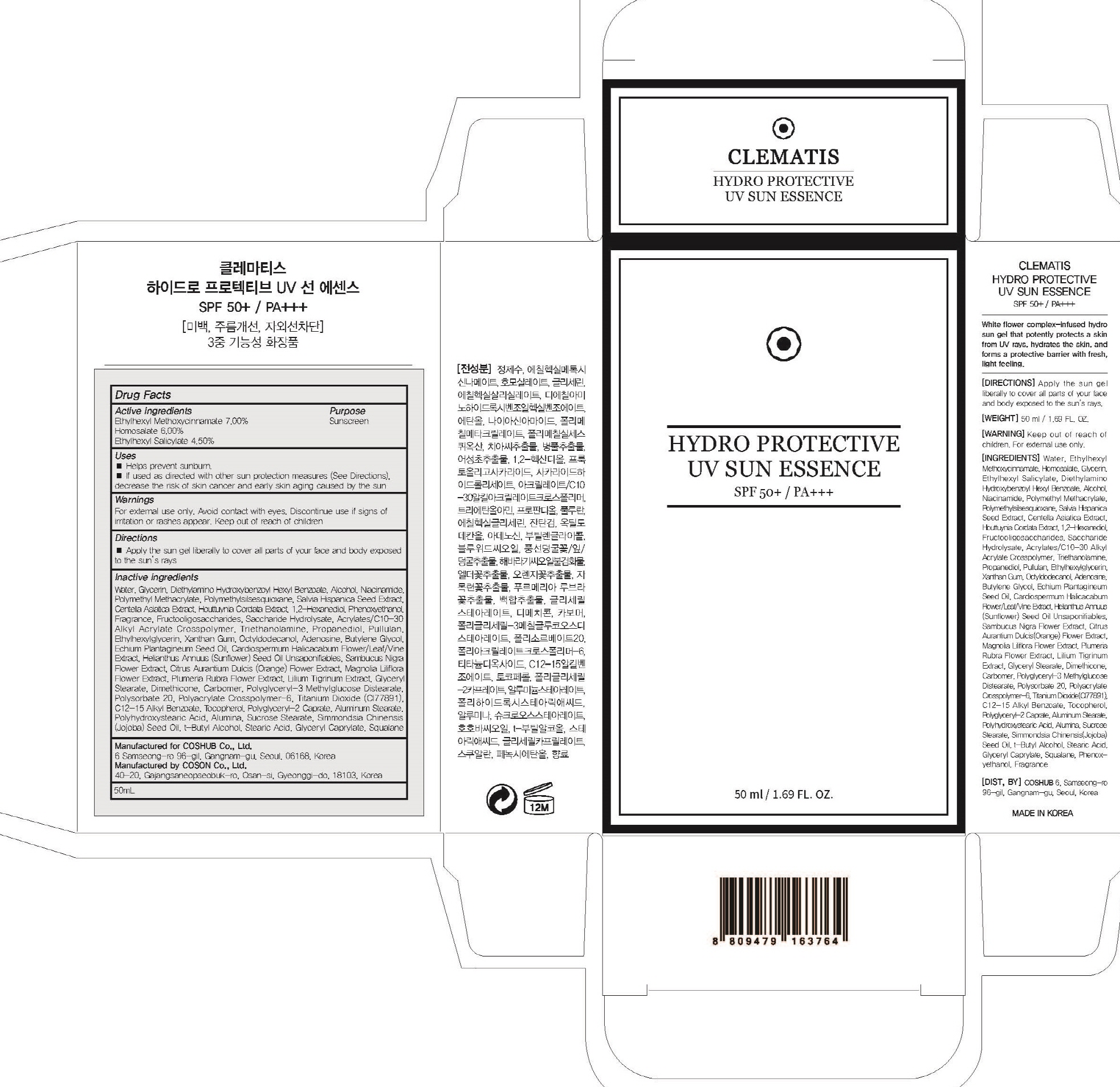 DRUG LABEL: CLEMATIS HYDRO PROTECTIVE UV SUN ESSENCE
NDC: 71702-060 | Form: GEL
Manufacturer: Coshub Co., Ltd.
Category: otc | Type: HUMAN OTC DRUG LABEL
Date: 20170905

ACTIVE INGREDIENTS: Octinoxate 3.50 g/50 mL; Homosalate 3.00 g/50 mL; Octisalate 2.25 g/50 mL
INACTIVE INGREDIENTS: Water; Glycerin

ACTIVE INGREDIENT

Active ingredients: Ethylhexyl Methoxycinnamate 7.00%, Homosalate 6.00%, Ethylhexyl Salicylate 4.50%

INACTIVE INGREDIENT

Inactive ingredients: Water, Glycerin, Diethylamino Hydroxybenzoyl Hexyl Benzoate, Alcohol, Niacinamide, Polymethyl Methacrylate, Polymethylsilsesquioxane, Salvia Hispanica Seed Extract, Centella Asiatica Extract, Houttuynia Cordata Extract, 1,2-Hexanediol, Phenoxyethanol, Fragrance, Fructooligosaccharides, Saccharide Hydrolysate, Acrylates/C10-30 Alkyl Acrylate Crosspolymer, Triethanolamine, Propanediol, Pullulan, Ethylhexylglycerin, Xanthan Gum, Octyldodecanol, Adenosine, Butylene Glycol, Echium Plantagineum Seed Oil, Cardiospermum Halicacabum Flower/Leaf/Vine Extract, Helianthus Annuus (Sunflower) Seed Oil Unsaponifiables, Sambucus Nigra Flower Extract, Citrus Aurantium Dulcis (Orange) Flower Extract, Magnolia Liliflora Flower Extract, Plumeria Rubra Flower Extract, Lilium Tigrinum Extract, Glyceryl Stearate, Dimethicone, Carbomer, Polyglyceryl-3 Methylglucose Distearate, Polysorbate 20, Polyacrylate Crosspolymer-6, Titanium Dioxide (CI77891), C12-15 Alkyl Benzoate, Tocopherol, Polyglyceryl-2 Caprate, Aluminum Stearate, Polyhydroxystearic Acid, Alumina, Sucrose Stearate, Simmondsia Chinensis (Jojoba) Seed Oil, t-Butyl Alcohol, Stearic Acid, Glyceryl Caprylate, Squalane

PURPOSE

Purpose: Sunscreen

WARNINGS

Warnings: For external use only. Avoid contact with eyes. Replace the cap after use. Discontinue use if signs of irritation or rashes appear. Keep out of reach of children.

DESCRIPTION

Uses: - Helps prevent sunburn. - If used as directed with other sun protection measures (See Directions), decrease the risk of skin cancer and early skin aging caused by the sun

Directions: Apply the sun gel liberally to cover all parts of your face and body exposed to the sun's rays.